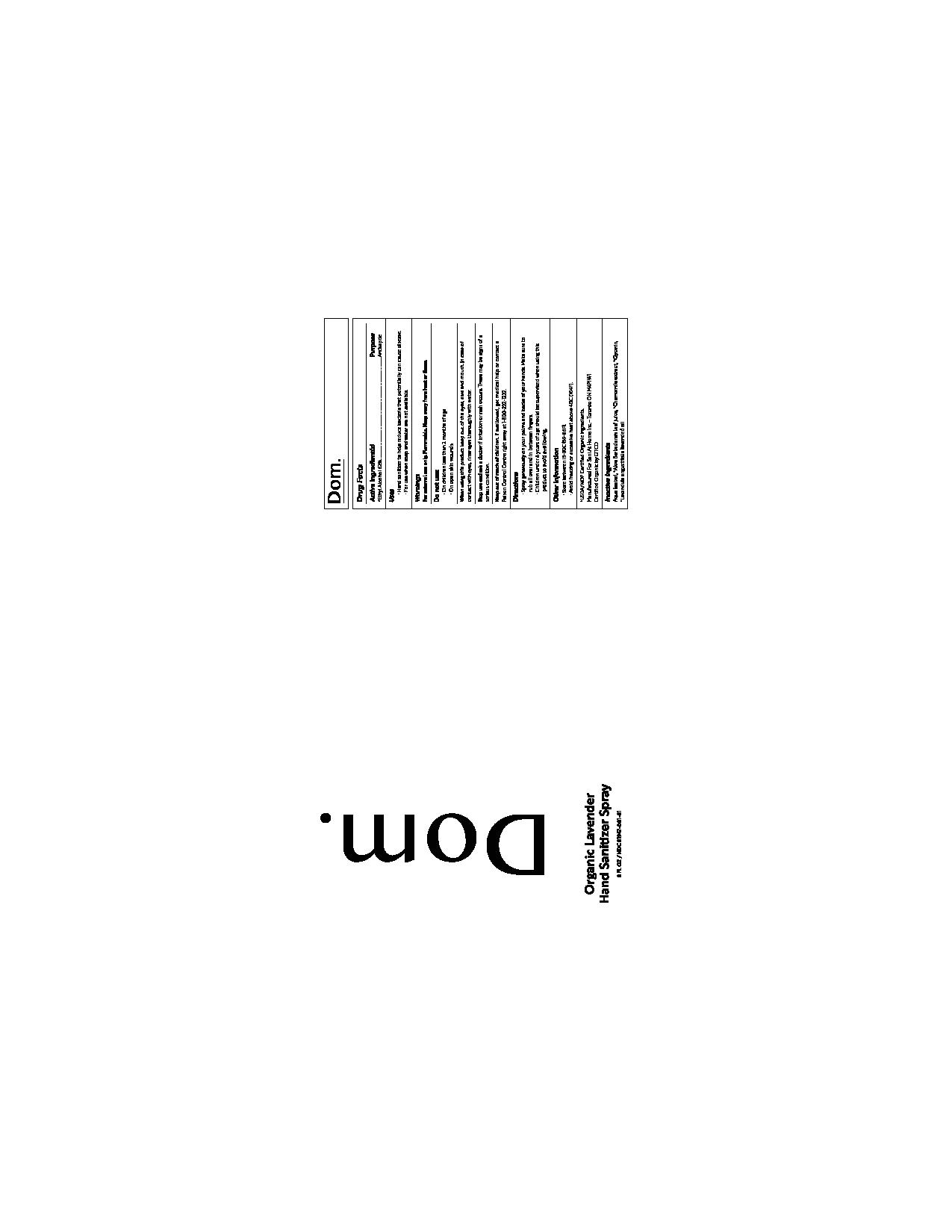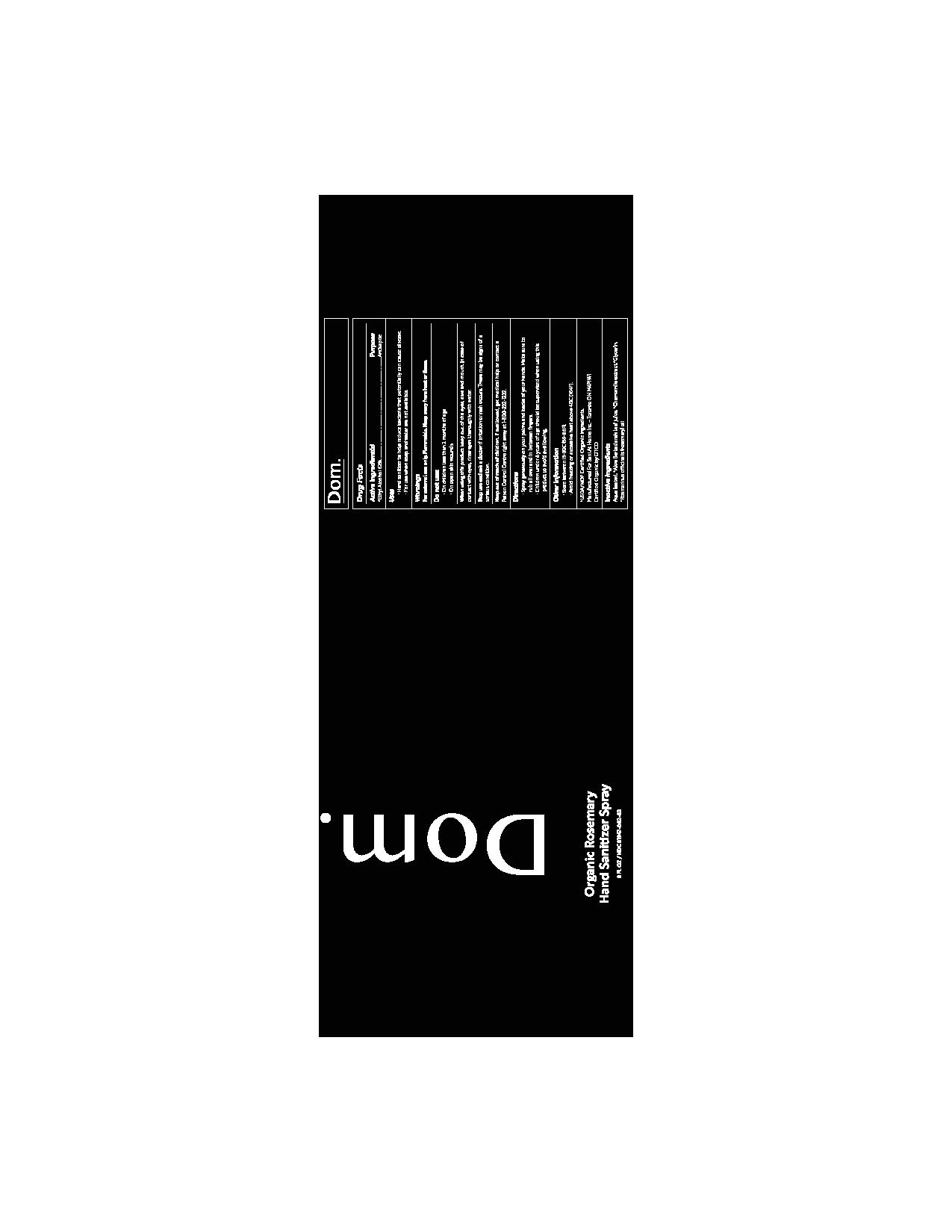 DRUG LABEL: Dom Organic Lavender Hand Sanitizer
NDC: 81947-001 | Form: SPRAY
Manufacturer: Sani At Home Inc.
Category: otc | Type: HUMAN OTC DRUG LABEL
Date: 20210412

ACTIVE INGREDIENTS: ALCOHOL 62.225 mL/100 mL
INACTIVE INGREDIENTS: ALOE VERA LEAF 0.01 mL/100 mL; GLYCERIN 3 mL/100 mL; LAVENDER OIL 0.63 mL/100 mL; WATER 34.12 mL/100 mL; CHAMAEMELUM NOBILE FLOWER 0.01 mL/100 mL

Active Ingredient(s)

Ethyl Alcohol 62%. Purpose: Antiseptic

Use

Hand Sanitizer to help reduce bacteria that potentially can cause disease. For use when soap and water are not available.

Warnings

For external use only. Flammable. Keep away from heat or flame

Do not use

- On children less than 2 months of age
- On open skin wounds

When using this product keep out of eyes, ears, and mouth. In case of contact with eyes, rinse eyes thoroughly with water.
Stop use and ask a doctor if irritation or rash occurs. These may be signs of a serious condition.
Keep out of reach of children. If swallowed, get medical help or contact a Poison Control Center right away at 1-800-222-1222.

Stop use and ask a doctor if irritation or rash occurs. These may be signs of a serious condition.

Keep out of reach of children. If swallowed, get medical help or contact a Poison Control Center right away at 1-800-222-1222.

Directions

- Spray generously on your palms and backs of your hands. Make sure to rub all over and in between fingers.
- Children under 6 years of age should be supervised when using this product to avoid swallowing.

Other information

- Store between 15-30C (59-86F)
- Avoid freezing and excessive heat above 40C (104F)

Inactive ingredients

Aqua (water), *Aloe Barbadensis leaf juice, *Chamomile extract, *Glycerin, *Rosmarinus offinalis (rosemary) oil

PURPOSE

Antiseptic